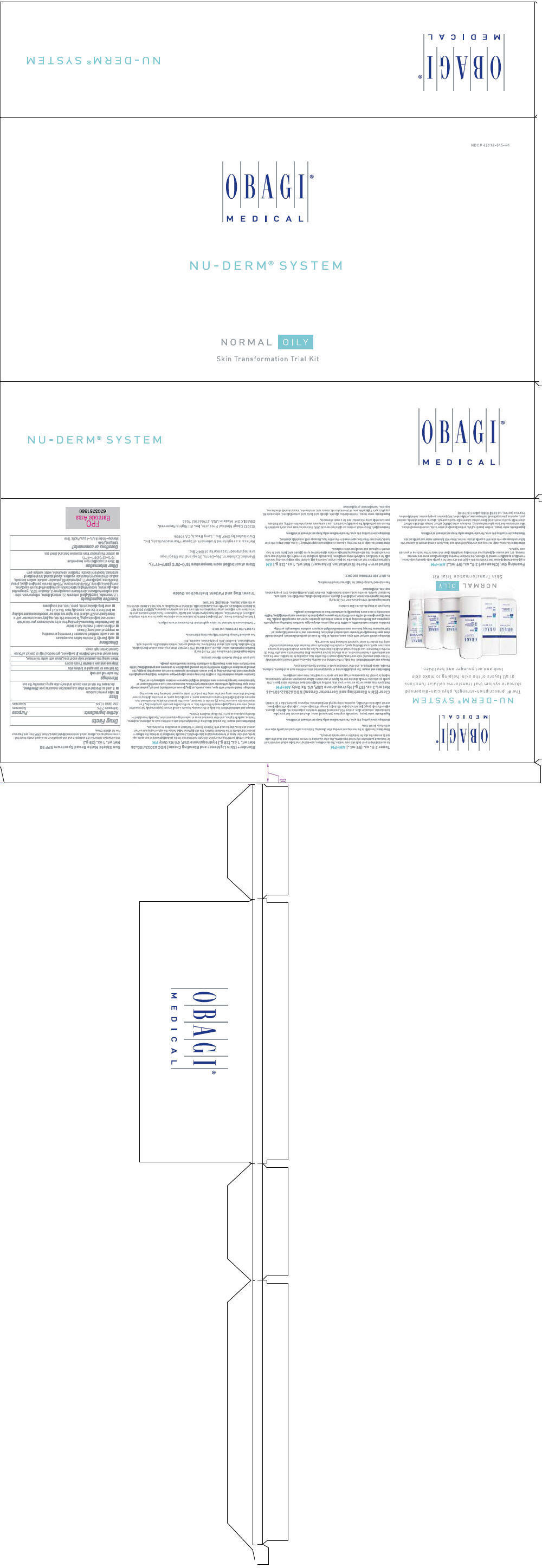 DRUG LABEL: nu-derm system normal-oily
NDC: 62032-515 | Form: KIT | Route: TOPICAL
Manufacturer: Obagi Cosmeceuticals LLC
Category: prescription | Type: HUMAN PRESCRIPTION DRUG LABEL
Date: 20191204

ACTIVE INGREDIENTS: HYDROQUINONE 40 mg/1 g; HYDROQUINONE 40 mg/1 g; OCTINOXATE 75 mg/1 g; ZINC OXIDE 105 mg/1 g
INACTIVE INGREDIENTS: EDETATE DISODIUM; PPG-2 MYRISTYL ETHER PROPIONATE; TROLAMINE SALICYLATE; SODIUM LAURYL SULFATE; CETYL ALCOHOL; GLYCERIN; LACTIC ACID, UNSPECIFIED FORM; .ALPHA.-TOCOPHEROL ACETATE; ASCORBIC ACID; SODIUM METABISULFITE; WATER; METHYLPARABEN; PROPYLPARABEN; BUTYLATED HYDROXYTOLUENE; PHENYL TRIMETHICONE; EDETATE DISODIUM; BUTYLPARABEN; STEARYL ALCOHOL; SODIUM LAURYL SULFATE; CETYL ALCOHOL; GLYCERIN; LACTIC ACID, UNSPECIFIED FORM; .ALPHA.-TOCOPHEROL ACETATE; ASCORBIC ACID; SODIUM METABISULFITE; WATER; METHYLPARABEN; PROPYLPARABEN; BUTYLATED HYDROXYTOLUENE; CYCLOMETHICONE 5; WATER; PEG-10 DIMETHICONE (600 CST); PENTYLENE GLYCOL; STEARYL ALCOHOL; POLYOXYL 20 CETOSTEARYL ETHER; PHENYL TRIMETHICONE; PEG-40 STEARATE; SODIUM DIHYDROXYCETYL PHOSPHATE; HYDROGENATED PALM GLYCERIDES; CITRIC ACID MONOHYDRATE; CETOSTEARYL ALCOHOL; .ALPHA.-TOCOPHEROL ACETATE; 1,2-HEXANEDIOL; CAPRYLYL GLYCOL; TROPOLONE; CHLORPHENESIN; XANTHAN GUM; POTASSIUM SORBATE; SODIUM BENZOATE; TETRAHEXYLDECYL ASCORBATE; UBIDECARENONE; EDETATE DISODIUM; METHYLISOTHIAZOLINONE; HYDROXYETHYL ACRYLATE/SODIUM ACRYLOYLDIMETHYL TAURATE COPOLYMER (100000 MPA.S AT 1.5%); SQUALANE; POLYSORBATE 60

NU-DERM® SYSTEM NORMAL-OILY
SKIN TRANSFORMATION TRIAL KIT

Foaming Gel (Cleanser) 2 fl. oz. (59 mL.) AM+PM

A gel-based facial cleanser that transforms into a light and airy foam for a gentle daily cleansing experience. Formulated specially for normal to oily skin, the Nu-Derm Foaming Gel deep-cleans pores and removes makeup, dirt, and excess oil, leaving your skin feeling completely clean and ready for the next step of your skin care regimen.

Directions

Use twice daily, morning and evening. Wet hands and face. Work a small amount of cleanser into lather and massage onto skin with a gentle circular motion. Rinse with lukewarm water and gently pat dry.

Warnings

Avoid getting into eyes. For external use only.

Ingredients

water (aqua), sodium laureth sulfate, sodium lauroyl oat amino acids, cocamidopropyl betaine, aloe barbadensis leaf juice (aloe barbadensis), medicago sativa (alfalfa) extract, borago officinalis extract, chamomilla recutita (matricaria) flower extract (chamomilla recutita extract), glycerin, sodium chloride, xanthan gum, saponins, phenoxyethanol, methylparaben, ethylparaben, butylparaben, propylparaben, isobutylparaben, fragrance (parfum), red 33 (CI 17200), yellow 5 (CI 19140)

Toner 2 fl. oz. (59 mL.) AM+PM

An essential step in your daily skin care routine, this alcohol-free, non-drying toner helps adjust your skin's pH for increased penetration of product ingredients. Use after cleansing to remove impurities and dead skin cells and to prepare the skin for hydration or appropriate products.

Directions

Use daily, in the morning and evening after cleansing. Saturate a cotton pad and gently wipe over entire face. Do not rinse.

Warnings

Avoid getting into eyes. For external use only.

Ingredients

water (aqua), hamamelis virginiana (witch hazel) water, aloe barbadensis leaf juice (aloe barbadensis), potassium alum, sodium PCA, panthenol, DMDM hydantoin, polysorbate 80, allantoin, glycerin, salvia officinalis (sage) leaf extract (salvia officinalis), borago officinalis extract, calendula officinalis flower extract (calendula officinalis), saponins, iodopropynyl butylcarbamate, fragrance (parfum), blue 1 (CI 42090)

Clear (Skin Bleaching and Corrector Cream) NDC 62032-101-36 Net wt. 2 oz. (57 g.) Hydroquinone USP, 4% Rx Only AM+PM

Dark spots may appear on the surface of your skin, but they actually start deep within the skin's layers. This gentle yet effective formula absorbs into the layers of your skin to deliver prescription-strength hydroquinone, helping to correct the appearance of age and sun spots for a healthier, more even complexion.

Indications and usage

The gradual bleaching of hyperpigmented skin conditions such as chloasma, melasma, freckles, senile lentigines, and other unwanted areas of melanin hyperpigmentation.

Dosage and administration

Use daily, in the morning and evening. Squeeze a small amount (approximately 1-2 pea-sized amounts) onto your hand. Apply evenly to the entire face, extending to the hairline, over the ears, and ending with a feathering motion, or as directed by your physician. If no improvement is seen after three (3) months of treatment, use of this product should be discontinued. Sun exposure should be limited by using a sunscreen agent, a sun blocking agent, or protective clothing to cover bleached skin when using and after using this product in order to prevent darkening from reoccurring.

Warnings

DO NOT USE

Avoid contact with eyes, nose, mouth, or lips. In case of accidental contact, patient should rinse eyes thoroughly with water and contact physician. Sunscreen use is an essential aspect of hydroquinone therapy because even minimal sunlight exposure sustains melanocytic activity.

Contains sodium metabisulfite, a sulfite that may cause allergic-type reactions including anaphylactic symptoms and life-threatening or less severe asthmatic episodes in certain susceptible people. The overall prevalence of sulfite sensitivity in the general population is unknown and probably low. Sulfite sensitivity is seen more frequently in asthmatic than in nonasthmatic people.

Each gram of Obagi Nu-Derm Clear contains:

Active ingredient

Hydroquinone USP, 4% (40 mg/g)

Inactive ingredients

water, cetyl alcohol, glycerin, sodium lauryl sulfate, stearyl alcohol, lactic acid, tocopheryl acetate, ascorbic acid, sodium metabisulfite, disodium EDTA, methylparaben, BHT, propylparaben, saponins, butylparaben

See enclosed Package Insert for full prescribing information.

Rx ONLY. FOR EXTERNAL USE ONLY.

Exfoderm® Forte (Exfoliation Enhancer) Net wt. 1 oz. (28 g.) AM

A lightweight lotion that exfoliates the top layer of skin, removing dull, old skin cells while promoting new skin cells for a revitalized, healthy-looking complexion. Specifically developed for normal to oily skin that may need more exfoliation, this skin-enhancing formula contains alpha-hydroxy acids (glycolic acid, lactic acid) to help smooth roughness and reveal your skin's radiance.

Directions

Use daily, in the morning. Squeeze a small amount (approximately 1-2 pea-sized drops) onto your hands. Using your fingertips, apply evenly to the entire face. Massage until completely absorbed.

Warnings

Avoid getting into eyes. For external use only.

Sunburn Alert

This product contains an alpha hydroxy acid (AHA) that may increase your skin's sensitivity to the sun and particularly the possibility of sunburn. Use a sunscreen, wear protective clothing, and limit sun exposure while using this product and for a week afterwards.

Ingredients

water (aqua), triethanolamine, glycerin, glycolic acid, lactic acid, cetearyl alcohol, polysorbate 60, caprylic/capric triglyceride, emu oil (dromiceius oil), stearic acid, cetyl alcohol, stearyl alcohol, dimethicone, saponins, methylparaben, propylparaben

Blender® (Skin Lightener and Blending Cream) NDC 62032-100-36 Net wt. 1 oz. (28 g.) Hydroquinone USP, 4% Rx Only PM

A unique formula containing prescription-strength hydroquinone for the gradual lightening of sun spots, age spots, and other types of hyperpigmentation (discoloration). Specially formulated to optimize the delivery of product ingredients in the Nu-Derm System, this skin lightener helps reduce the signs of aging and correct uneven skin tone. May be used with Tretinoin Cream [Tretinoin cream is indicated for topical application in the treatment of acne vulgaris.] or Refissa [Refissa [Tretinoin Cream, USP (Emollient) 0.05%] is indicated as an adjunctive agent for use in the mitigation (palliation) of fine wrinkles, mottled hyperpigmentation, and tactile roughness of facial skin in patients who do not achieve such palliation using comprehensive skin care and sun avoidance programs. REFISSA DOES NOT ELIMINATE WRINKLES, REPAIR SUN-DAMAGED SKIN, REVERSE PHOTOAGING, or RESTORE A MORE YOUTHFUL or YOUNGER DERMAL HISTOLOGIC PATTERN.] as prescribed by a physician.

Indications and usage

The gradual bleaching of hyperpigmented skin conditions such as chloasma, melasma, freckles, senile lentigines, and other unwanted areas of melanin hyperpigmentation. Specially formulated for blending purposes as part of the Obagi Nu-Derm System.

Dosage and administration

Use daily, in the evening. Squeeze a small amount (approximately 1-2 pea-sized drops) onto your hand. Apply evenly to the entire face, or as directed by your skin care physician. If no improvement is seen after three (3) months of treatment, use of this product should be discontinued. Sun exposure should be limited by using a sunscreen agent, a sun blocking agent, or protective clothing to cover bleached skin when using and after using this product in order to prevent darkening from reoccurring.

Warnings

DO NOT USE

Avoid contact with eyes, nose, mouth, or lips. In case of accidental contact, patient should rinse eyes thoroughly with water and contact physician. Sunscreen use is an essential aspect of hydroquinone therapy because even minimal sunlight exposure sustains melanocytic activity.

Contains sodium metabisulfite, a sulfite that may cause allergic-type reactions including anaphylactic symptoms and life-threatening or less severe asthmatic episodes in certain susceptible people. The overall prevalence of sulfite sensitivity in the general population is unknown and probably low. Sulfite sensitivity is seen more frequently in asthmatic than in nonasthmatic people.

Each gram of Obagi Nu-Derm Blender contains

Active ingredient

Hydroquinone USP, 4% (40 mg/g)

Inactive ingredients

water, glycerin, cetyl alcohol, PPG-2 myristyl ether propionate, sodium lauryl sulfate, TEA-salicylate, lactic acid, phenyl trimethicone, tocopheryl acetate, sodium metabisulfite, ascorbic acid, methylparaben, disodium EDTA, propylparaben, saponins, BHT

See enclosed Package Insert for full prescribing information.

Rx ONLY. FOR EXTERNAL USE ONLY.

Travel Bag and Patient Insruction Guide

STORAGE AND HANDLING

Store at controlled room temperature 15°C–25°C (59°F–77°F).

STORAGE AND HANDLING

Blender, Exfoderm, Nu-Derm, Obagi and the Obagi logo are registered treademarks of OMP, Inc.

Refissa is a registered trademark of Spear Pharmaceuticals, Inc.
Distributed by OMP, Inc., Long Beach, CA 90806

©2012 Obagi Medical Produts, Inc. All RIghts Reserved.
OBAGI.COM Made in USA 41706410Z 7064

Sun Shield Matte Broad Spectrum SPF 50 Net wt. 1 oz. (28 g.)

This sunscreen combines UVB absorption and UVA protection in an elegant, matte finish that is non-comedogenic, allergy tested, and dermatologist tested. Sheer, PABA free, and fragrance free for all skin types.

Drug Facts

ACTIVE INGREDIENT

Active ingredients | Purpose
Octinoxate 7.5% | Sunscreen
Zinc Oxide 10.5% | Sunscreen

Uses

- helps prevent sunburn
- if used as directed with other sun protection measures (see Directions), decreases the risk of skin cancer and early skin aging caused by the sun

Warnings

For external use only

Do not use on damaged or broken skin

Stop use and ask a doctor if rash occurs

When using this product keep out of eyes. Rinse with water to remove.

Keep out of reach of children. If swallowed, get medical help or contact a Poison Control Center right away.

Directions

- apply liberally 15 minutes before sun exposure
- use a water resistant sunscreen if swimming or sweating
- reapply at least every 2 hours
- children under 6 months: Ask a doctor
- Sun Protection Measures. Spending time in the sun increases your risk of skin cancer and early skin aging. To decrease this risk, regularly use a sunscreen with a Broad Spectrum SPF value of 15 or higher and other sun protection measures including:
  - limit time in the sun, especially from 10 a.m.-2 p.m.
  - wear long-sleeved shirts, pants, hats, and sunglasses

Inactive ingredients

1,2-hexanediol, caprylyl glycol, ceteareth-20, cetearyl alcohol, chlorphenesin, citric acid, cyclopentasiloxane, dimethicone crosspolymer-3, disodium EDTA, hydrogenated palm glycerides, hydroxyethyl acrylate/sodium acryloyldimethyl taurate copolymer, methylisothiazolinone, PEG-10 dimethicone, PEG-40 stearate, pentylene glycol, phenyl trimethicone, polysilicone-11, polysorbate 60, potassium sorbate, sodium benzoate, sodium dihydroxycetyl phosphate, squalane, stearyl alcohol, tetrahexyldecyl ascorbate, tocopheryl acetate, tropolone, ubiquinone, water, xanthan gum

Other information

- Store at controlled room temperature:
  15°C–25°C (59°F–77°F)
- protect this product from excessive heat and direct sun

Questions or comments?

1.800.636.7546
Monday–Friday 9 a.m.-4 p.m. Pacific Time

PRINCIPAL DISPLAY PANEL - Kit Carton

NDC# 62032-515-60

OBAGI®
MEDICAL

NU-DERM® SYSTEM

NORMAL OILY

Skin Transformation Trial Kit